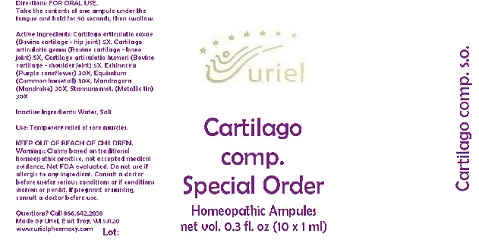 DRUG LABEL: Cartilago comp. Special Order
NDC: 48951-3201 | Form: LIQUID
Manufacturer: Uriel Pharmacy Inc.
Category: homeopathic | Type: HUMAN OTC DRUG LABEL
Date: 20180516

ACTIVE INGREDIENTS: BOS TAURUS CARTILAGE 5 [hp_X]/1 mL; ECHINACEA, UNSPECIFIED 30 [hp_X]/1 mL; EQUISETUM ARVENSE TOP 30 [hp_X]/1 mL; MANDRAGORA OFFICINARUM ROOT 30 [hp_X]/1 mL; TIN 30 [hp_X]/1 mL
INACTIVE INGREDIENTS: WATER; SODIUM CHLORIDE

Cartilago comp. Special Order

INDICATIONS AND USAGE

Directions: FOR ORAL USE.

DOSAGE AND ADMINISTRATION

Take the contents of one ampule under the tongue and hold for 30 seconds, then swallow.

ACTIVE INGREDIENT

Active Ingredients: Cartilago articulatio coxae 5X, Cartilago articulatio genus 5X, Cartilago articulatio humeri 5X, Echinacea e pl. tota 30X, Equisetum ex herba 30X, Mandragora e rad. 30X, Stannum metallicum 30X

Inactive Ingredients: Water, Salt

PURPOSE

Use: Temporary relief of sore muscles.

KEEP OUT OF REACH OF CHILDREN.

WARNINGS

Warnings: Claims based on traditional homeopathic practice, not accepted medical evidence. Not FDA evaluated. Do not use if allergic to any ingredient. Consult a doctor before usefor serious conditions or if conditions worsen or persist. If pregnant or nursing, consult a doctor before use.

QUESTIONS

Questions? Call 866.642.2858 Made by Uriel, East Troy, WI 53120 www.urielpharmacy.com